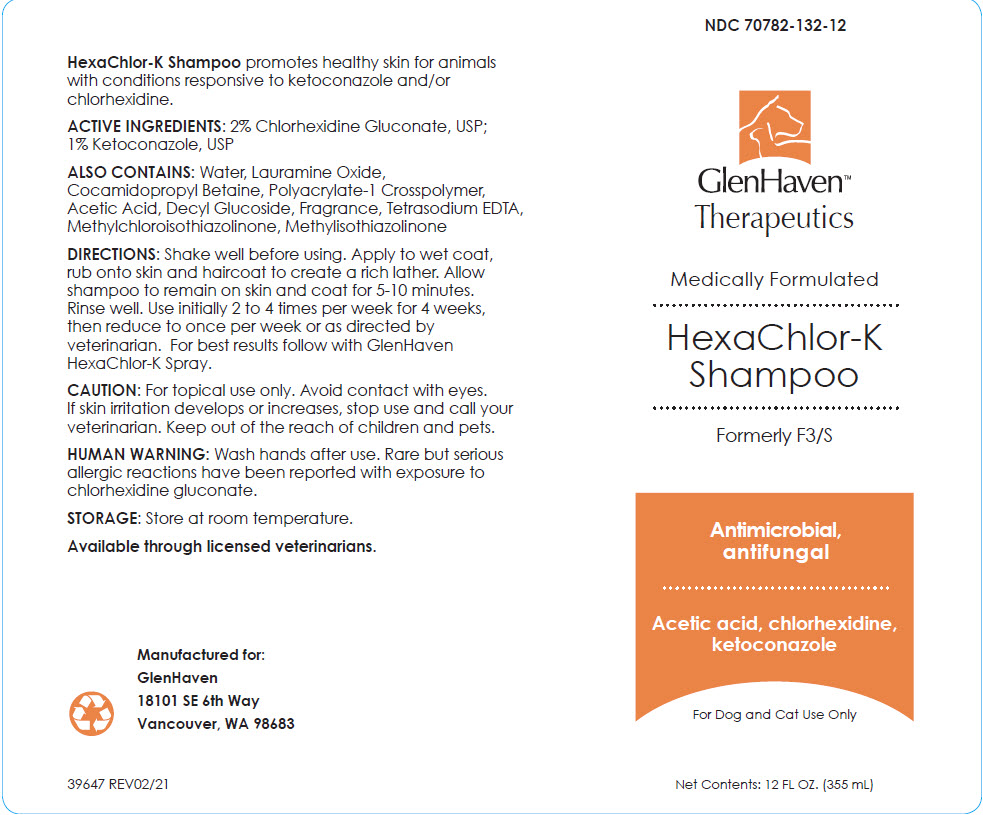 DRUG LABEL: Hexachlor-K
NDC: 70782-132 | Form: SHAMPOO, SUSPENSION
Manufacturer: GlenHaven LLC
Category: animal | Type: OTC ANIMAL DRUG LABEL
Date: 20211208

ACTIVE INGREDIENTS: CHLORHEXIDINE GLUCONATE 20 mg/1 mL; KETOCONAZOLE 10 mg/1 mL
INACTIVE INGREDIENTS: WATER; LAURAMINE OXIDE; COCAMIDOPROPYL BETAINE; CARBOMER INTERPOLYMER TYPE A (ALLYL SUCROSE CROSSLINKED); ACETIC ACID; DECYL GLUCOSIDE; EDETATE SODIUM; METHYLCHLOROISOTHIAZOLINONE; METHYLISOTHIAZOLINONE

Hexachlor-K Shampoo

VETERINARY INDICATIONS

HexaChlor-K Shampoo promotes healthy skin for animals with conditions responsive to ketoconazole and/or chlorhexidine.

DESCRIPTION

ACTIVE INGREDIENTS: 2% Chlorhexidine Gluconate, USP; 1% Ketoconazole, USP

ALSO CONTAINS: Water, Lauramine Oxide, Cocamidopropyl Betaine, Polyacrylate-1 Crosspolymer, Acetic Acid, Decyl Glucoside, Fragrance, Tetrasodium EDTA, Methylchloroisothiazolinone, Methylisothiazolinone

DOSAGE AND ADMINISTRATION

DIRECTIONS: Shake well before using. Apply to wet coat, rub onto skin and haircoat to create a rich lather. Allow shampoo to remain on skin and coat for 5-10 minutes. Rinse well. Use initially 2 to 4 times per week for 4 weeks, then reduce to once per week or as directed by veterinarian. For best results follow with GlenHaven HexaChlor-K Spray.

WARNINGS

CAUTION: For topical use only. Avoid contact with eyes. If skin irritation develops or increases, stop use and call your veterinarian. Keep out of the reach of children and pets.

HUMAN WARNING: Wash hands after use. Rare but serious allergic reactions have been reported with exposure to chlorhexidine gluconate.

HOW SUPPLIED

STORAGE: Store at room temperature.

Available through licensed veterinarians.

Manufactured for:
GlenHaven
18101 SE 6th Way
Vancouver, WA 98683

39647 REV02/21

PRINCIPAL DISPLAY PANEL - 355 mL Bottle Label

NDC 70782-132-12

GlenHaven™
Therapeutics

Medically Formulated

HexaChlor-K
Shampoo

Formerly F3/S

Antimicrobial,
antifungal

Acetic acid, chlorhexidine,
ketoconazole

For Dog and Cat Use Only

Net Contents: 12 FL OZ. (355 mL)